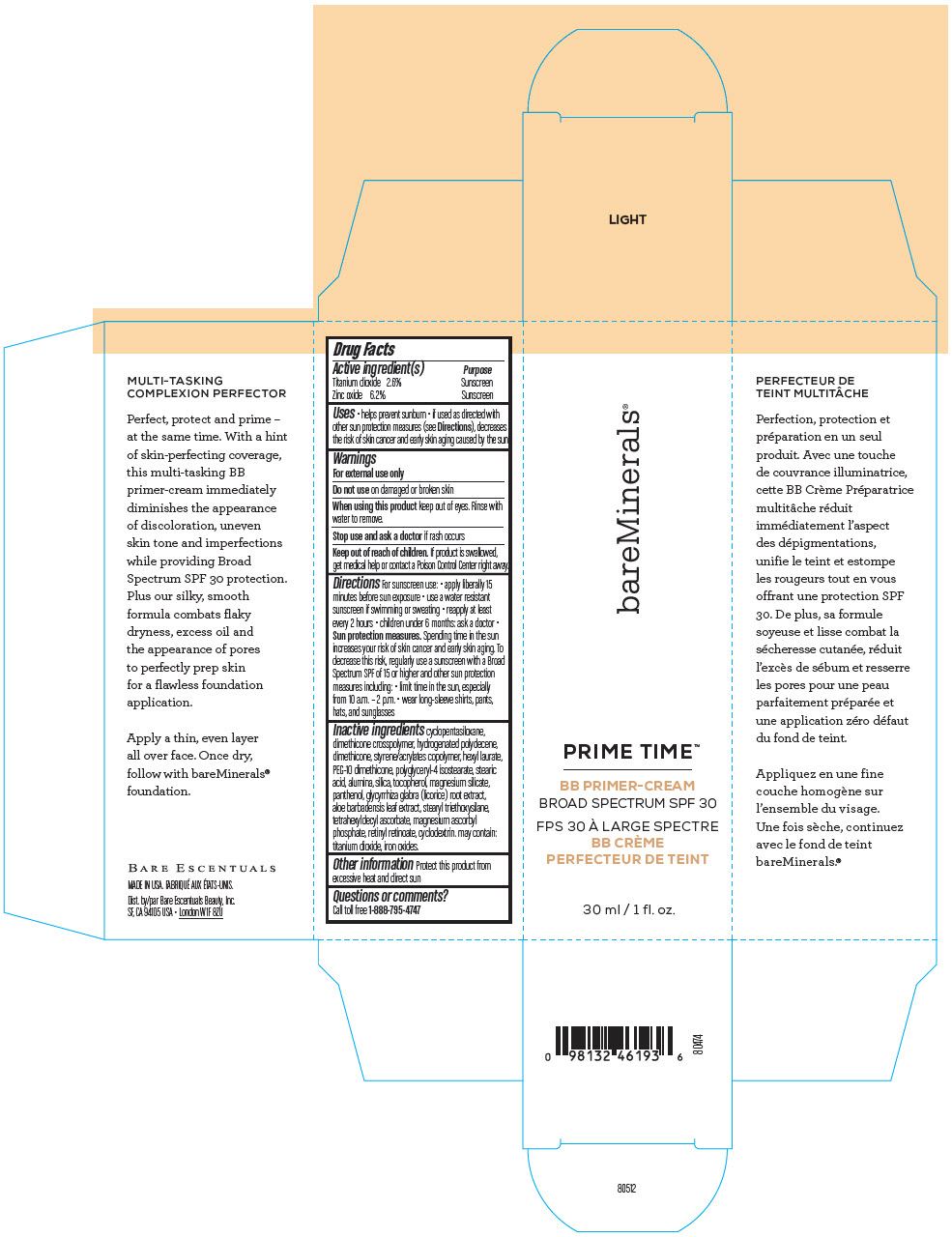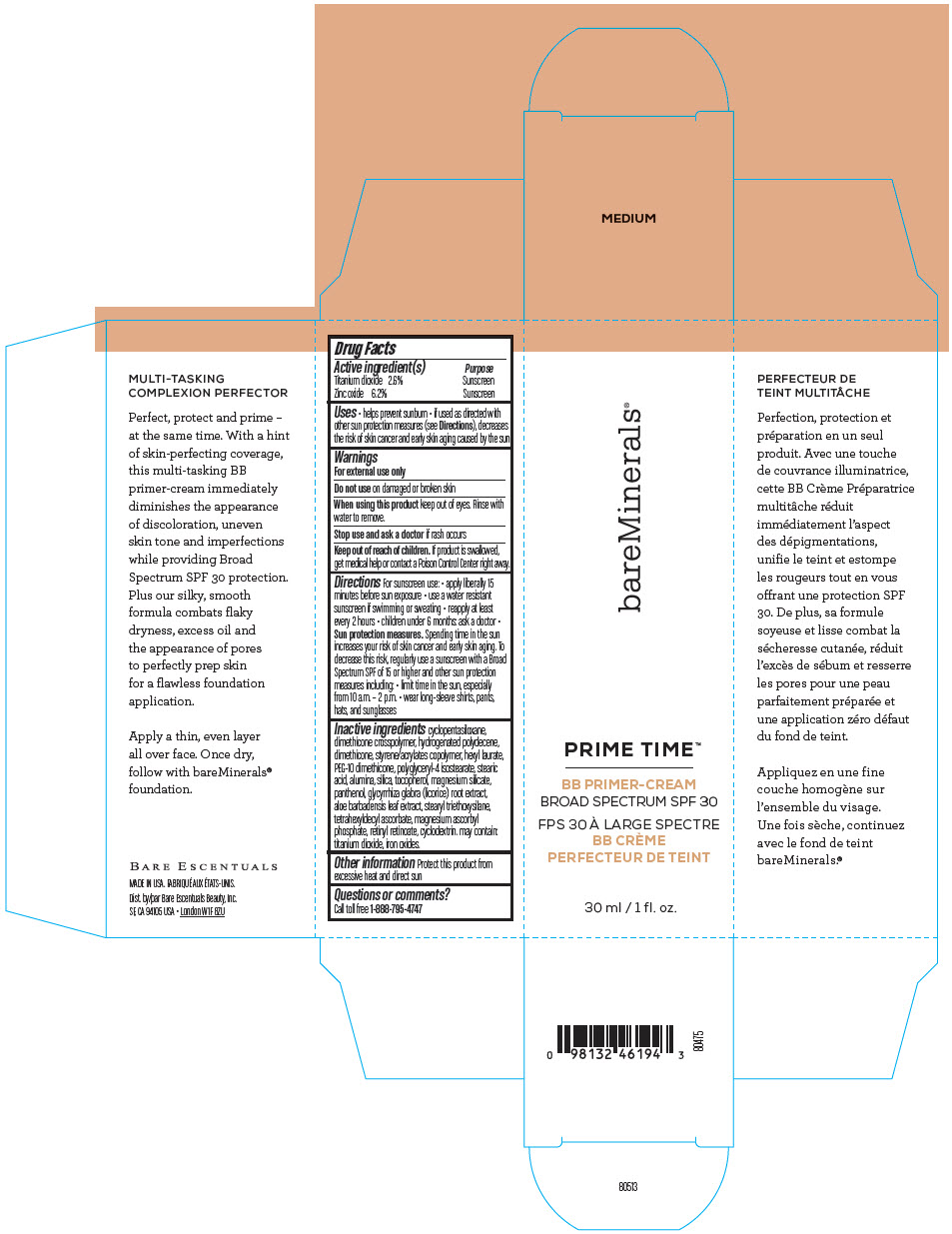 DRUG LABEL: bareMinerals Prime Time BB Primer-Cream Broad Spectrum SPF 30
NDC: 98132-004 | Form: CREAM
Manufacturer: Orveon Global US LLC
Category: otc | Type: HUMAN OTC DRUG LABEL
Date: 20231004

ACTIVE INGREDIENTS: TITANIUM DIOXIDE 780 mg/30 mL; ZINC OXIDE 1860 mg/30 mL
INACTIVE INGREDIENTS: CYCLOMETHICONE 5; DIMETHICONE CROSSPOLYMER (450000 MPA.S AT 12% IN CYCLOPENTASILOXANE); HYDROGENATED POLYDECENE TYPE I; DIMETHICONE; STYRENE/ACRYLAMIDE COPOLYMER (500000 MW); HEXYL LAURATE; POLYGLYCERYL-4 ISOSTEARATE; FERRIC OXIDE RED; PEG-10 DIMETHICONE (600 CST); STEARIC ACID; ALUMINUM OXIDE; FERRIC OXIDE YELLOW; SILICON DIOXIDE; GLYCYRRHIZA GLABRA; ALOE VERA LEAF; TOCOPHEROL; PANTHENOL; MAGNESIUM SILICATE; FERROSOFERRIC OXIDE; STEARYL TRIETHOXYSILANE; MAGNESIUM ASCORBYL PHOSPHATE; TETRAHEXYLDECYL ASCORBATE; RETINYL RETINOATE; CYCLODEXTRINS

bareMinerals® Prime Time™ BB Primer-Cream Broad Spectrum SPF 30

Drug Facts

ACTIVE INGREDIENT

Active ingredient(s) | Purpose
Titanium dioxide 2.6% | Sunscreen
Zinc oxide 6.2% | Sunscreen

Uses

- helps prevent sunburn
- if used as directed with other sun protection measures (see Directions), decreases the risk of skin cancer and early skin aging caused by the sun

Warnings

For external use only

Do not use on damaged or broken skin

When using this product keep out of eyes. Rinse with water to remove.

Stop use and ask a doctor if rash occurs

Keep out of reach of children. If product is swallowed, get medical help or contact a Poison Control Center right away.

Directions

For sunscreen use:

- apply liberally 15 minutes before sun exposure
- use a water resistant sunscreen if swimming or sweating
- reapply at least every 2 hours
- children under 6 months: ask a doctor
- Sun protection measures. Spending time in the sun increases your risk of skin cancer and early skin aging. To decrease this risk, regularly use a sunscreen with a Broad Spectrum SPF of 15 or higher and other sun protection measures including:
- limit time in the sun, especially from 10 a.m. – 2 p.m.
- wear long-sleeve shirts, pants, hats, and sunglasses

Inactive ingredients

cyclopentasiloxane, dimethicone crosspolymer, hydrogenated polydecene, dimethicone, styrene/acrylates copolymer, hexyl laurate, PEG-10 dimethicone, polyglyceryl-4 isostearate, stearic acid, alumina, silica, tocopherol, magnesium silicate, panthenol, glycyrrhiza glabra (licorice) root extract, aloe barbadensis leaf extract, stearyl triethoxysilane, tetrahexyldecyl ascorbate, magnesium ascorbyl phosphate, retinyl retinoate, cyclodextrin. may contain: titanium dioxide, iron oxides.

Other information

Protect this product from excessive heat and direct sun

Questions or comments?

Call toll free 1-888-795-4747

Dist. by Bare Escentuals Beauty, Inc.
SF, CA 94105 USA

PRINCIPAL DISPLAY PANEL - 30 ml Bottle Carton - Light

bareMinerals®

PRIME TIME™

BB PRIMER-CREAM
BROAD SPECTRUM SPF 30

30 ml / 1 fl. oz.

PRINCIPAL DISPLAY PANEL - 30 ml Bottle Carton - Medium

bareMinerals®

PRIME TIME™

BB PRIMER-CREAM
BROAD SPECTRUM SPF 30

30 ml / 1 fl. oz.